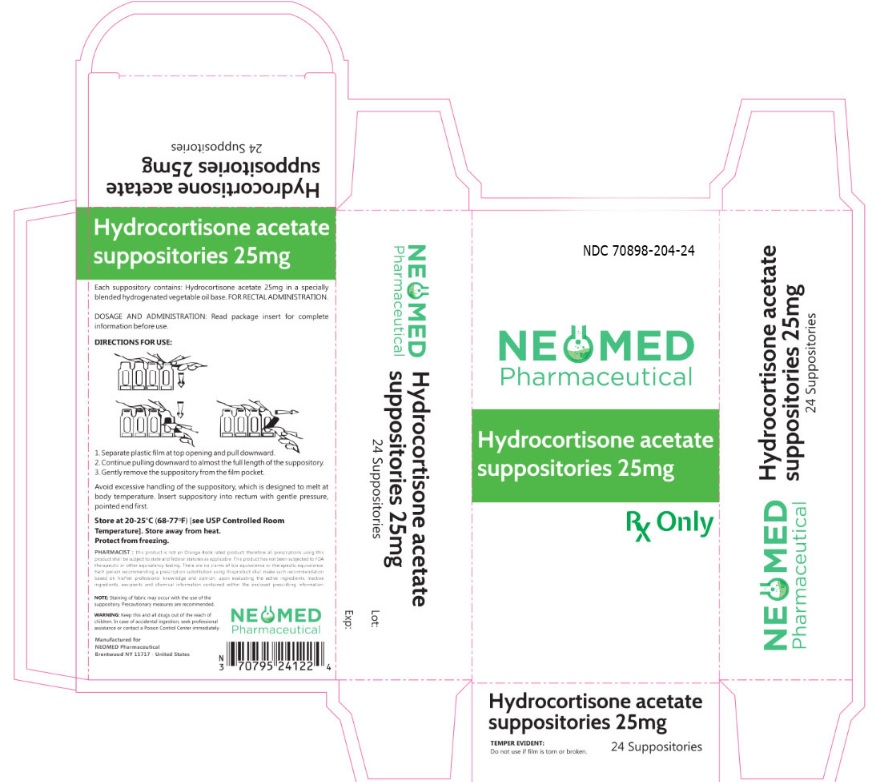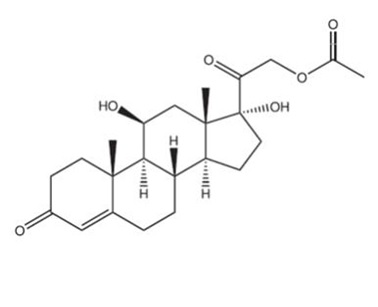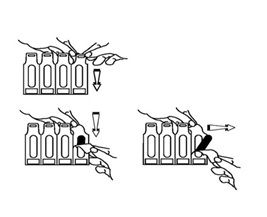 DRUG LABEL: Neomed Pharmaceutical
NDC: 70898-204 | Form: SUPPOSITORY
Manufacturer: Neomed Pharmaceutical
Category: prescription | Type: HUMAN PRESCRIPTION DRUG LABEL
Date: 20180305

ACTIVE INGREDIENTS: HYDROCORTISONE ACETATE 25 mg/1 1
INACTIVE INGREDIENTS: HYDROGENATED COCO-GLYCERIDES

Hydrocortisone acetate suppositories 25mg

Hydrocortisone acetate suppositories 25mg
For Rectal Administration
Rx Only

DESCRIPTION:

Hydrocortisone acetate is a corticosteroid designed chemically as pregn-4-ene 3, 20-dione, 21- (acetyloxy)-11, 17-dihydroxy––(11 β) with the following structural formula:

Each rectal suppository contains hydrocortisone acetate, USP 25 mg in a specially blended hydrogenated vegetable oil base.

CLINICAL PHARMACOLOGY:

In normal subjects, about 26% of hydrocortisone acetate is absorbed when the suppository is applied to the rectum. Absorption of hydrocortisone acetate may vary across abraded or inflamed surfaces. Topical steroids are primarily effective because of their anti-inflammatory, anti-pruritic and vasoconstrictive action.

INDICATIONS AND USAGE:

Hydrocortisone suppositories are indicated for use in:

- inflamed hemorrhoids
- post-irradiation (factitial) proctitis
- as an adjunct in the treatment of chronic ulcerative colitis
- cryptitis
- other inflammatory conditions of anorectum and pruritus ani.

CONTRAINDICATIONS:

Hydrocortisone suppositories are contraindicated in those patients having a history of hypersensitivity to hydrocortisone acetate or any of the components.

PRECAUTIONS:

Do not use Hydrocortisone suppositories unless adequate proctologic examination is made. If irritation develops, the product should be discontinued and appropriate therapy instituted. In the presence of an infection, the use of an appropriate antifungal or antibacterial agent should be instituted. If a favorable response does not occur promptly, Hydrocortisone suppository should be discontinued until the infection has been adequately controlled.

Carcinogenesis:

No long term studies in animals have been performed to evaluate the carcinogenic potential of corticosteroid suppositories.

Pregnancy Category C:

In laboratory animals, topical steroids have been associated with an increase in the incidence of fetal abnormalities when gestating females have been exposed to rather low dosage levels. There are no adequate and well controlled studies in pregnant women. Hydrocortisone suppositories should only be used during pregnancy if the potential benefit justifies the risk to the fetus. Drugs of this class should not be used extensively on pregnant patients, in large amounts, or for prolonged periods of time.

It is not known whether this drug is excreted in human milk and because many drugs are excreted in human milk and because of the potential for serious adverse reactions in nursing infants from Hydrocortisone suppositories, a decision should be made whether to discontinue nursing or to discontinue the drug, taking into account the importance of the drug to the mother

ADVERSE REACTIONS:

The following local adverse reactions have been reported with corticosteroid suppositories; burning, itching, irritation, dryness, folliculitis, hypopigmentation, allergic contact dermatitis, secondary infection.

To report suspected adverse reactions,
Contact NEOMED pharmaceutical or www.fda.gov/medwatch

Drug abuse and dependence have not been reported in patients treated with Hydrocortisone suppositories.

OVERDOSAGE:

If signs and symptoms of systemic over dosage occur, discontinue use.

DOSAGE AND ADMINISTRATION:

For Rectal administration.

OPENING INSTRUCTIONS

1. Separate plastic film at top opening and pull downward.
2. Continue pulling downward to almost the full length of the suppository.
3. Gently remove the suppository from the film pocket

Avoid excessive handling of the suppository which is designed to melt at body temperature. Insert suppository into the rectum with gentle pressure, pointed end first. Insert one suppository in the rectum twice daily, morning and night for two weeks, in nonspecific proctitis. In more severe cases, one suppository three times a day or two suppositories twice daily. In factitial proctitis, the recommended duration of therapy is six to eight weeks or less, according to the response of the individual case.

All prescription substitutions and/or recommendations using this product shall be made subject to state and federal statutes as applicable.

PLEASE NOTE: This is not an Orange Book product and has not been subjected to FDA therapeutic or other equivalency testing. No representation is made as to generic status or bio equivalency. Each person recommending a prescription substitution using this product shall make such recommendation based on his/her professional knowledge and opinion, upon evaluating the active ingredients, inactive ingredients, excipients and chemical information provided herein.

HOW SUPPLIED:

Hydrocortisone acetate suppositories 25mg are off-white, smooth surfaced and bullet shaped with one pointed end.

Box of 24 suppositories, NDC 70898-204-24

STORAGE:

Store at 20º-25ºC (68º-77ºF) [See USP Controlled Room Temperature]. Excursions permitted to 15º- 30ºC (59º-86ºF). Store away from heat. Protect from freezing

Other Information

Manufactured for:
NEOMED PHARMACEUTICAL
BRENTWOOD, NY 11717

Principal Display Panel

NDC: 70898-204-24

NEOMED Phamaceutical
Hydrocortisone acetate suppositories 25 mg

Rx Only

24 Suppositories

TEMPER EVIDENT:

Do not use if film is tore or broken